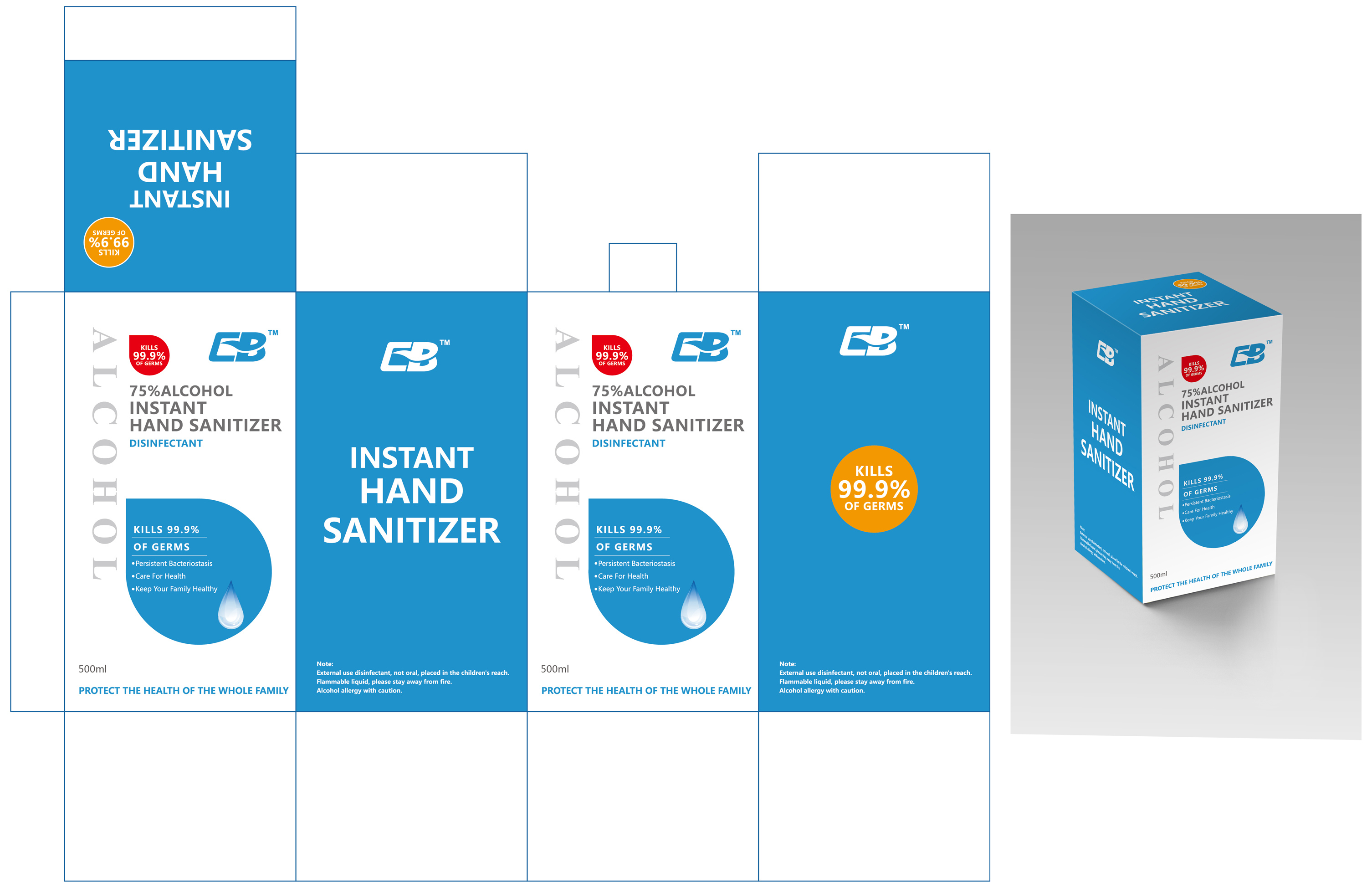 DRUG LABEL: Disposable hand fluid
NDC: 54800-001 | Form: LIQUID
Manufacturer: Longgang Chengbao Industry Co., Ltd.
Category: otc | Type: HUMAN OTC DRUG LABEL
Date: 20200618

ACTIVE INGREDIENTS: ALCOHOL 10.8 mL/60 mL
INACTIVE INGREDIENTS: WATER; CAMELLIA OIL; GLYCERIN

PURPOSE

Disinfection
Sterilization
No Rinseing

WARNINGS

Alcohol allergy with caution.

ACTIVE INGREDIENT

alcohol

INACTIVE INGREDIENT

water ,glycerine, tea ,DM831

INDICATIONS AND USAGE

External use disinfectant, not oral,

DOSAGE AND ADMINISTRATION

Flammable liquid, please stay away from fire.

keep out of reach of children